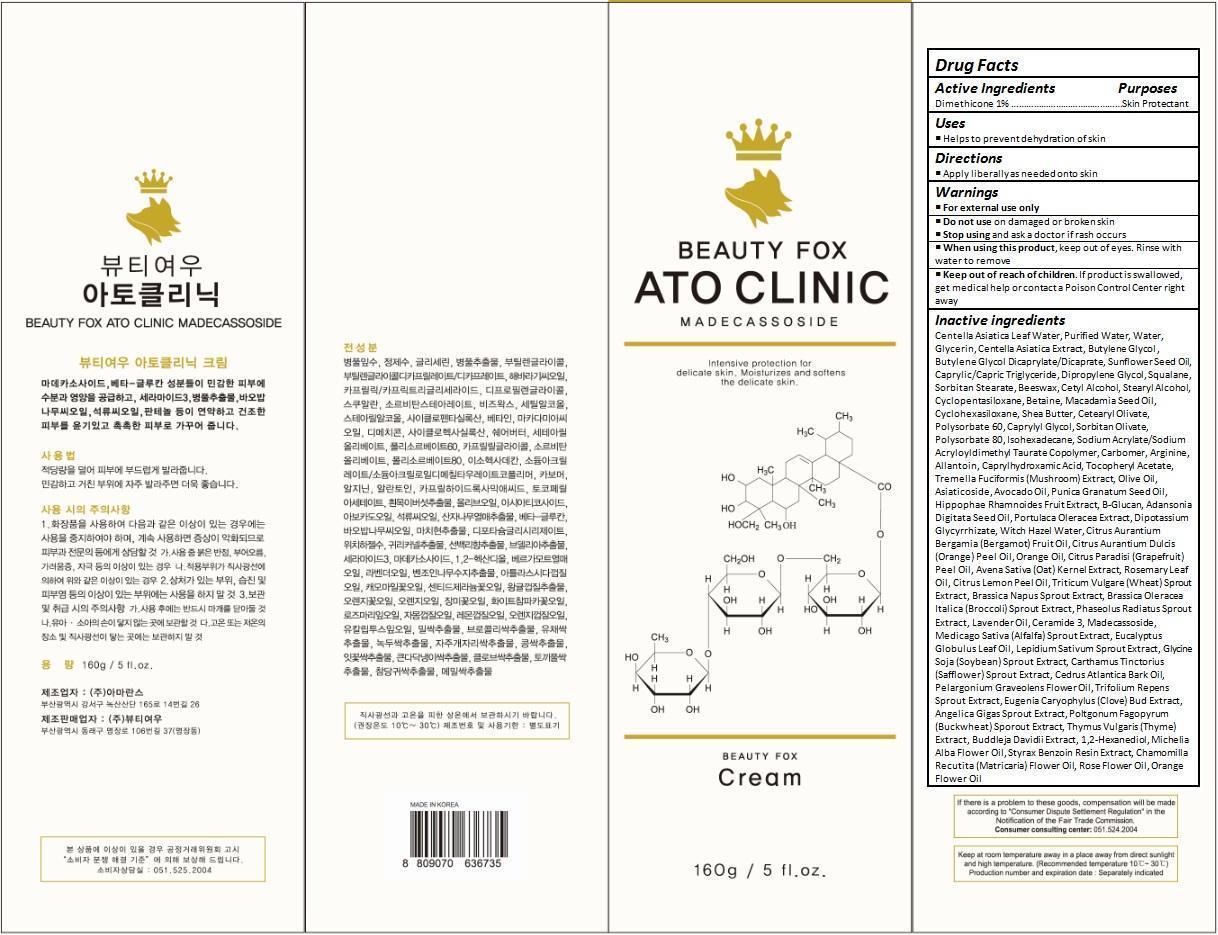 DRUG LABEL: BEAUTY FOX ATOCLINIC
NDC: 70129-001 | Form: CREAM
Manufacturer: Beauty Fox Co., Ltd.
Category: otc | Type: HUMAN OTC DRUG LABEL
Date: 20150930

ACTIVE INGREDIENTS: DIMETHICONE 1.6 g/160 g
INACTIVE INGREDIENTS: CENTELLA ASIATICA LEAF; WATER; GLYCERIN; CENTELLA ASIATICA; BUTYLENE GLYCOL; BUTYLENE GLYCOL DICAPRYLATE/DICAPRATE; SUNFLOWER OIL; MEDIUM-CHAIN TRIGLYCERIDES; DIPROPYLENE GLYCOL; SQUALANE; SORBITAN MONOSTEARATE; YELLOW WAX; CETYL ALCOHOL; STEARYL ALCOHOL; CYCLOMETHICONE 5; BETAINE; MACADAMIA OIL; CYCLOMETHICONE 6; SHEA BUTTER; CETEARYL OLIVATE; POLYSORBATE 60; CAPRYLYL GLYCOL; SORBITAN OLIVATE; POLYSORBATE 80; ISOHEXADECANE; SODIUM ACRYLATE/SODIUM ACRYLOYLDIMETHYLTAURATE COPOLYMER (4000000 MW); CARBOMER HOMOPOLYMER TYPE C (ALLYL PENTAERYTHRITOL CROSSLINKED); ARGININE; ALLANTOIN; CAPRYLHYDROXAMIC ACID; .ALPHA.-TOCOPHEROL ACETATE; CULTIVATED MUSHROOM; OLIVE OIL; ASIATICOSIDE; AVOCADO OIL; POMEGRANATE SEED OIL; HIPPOPHAE RHAMNOIDES FRUIT; CURDLAN; ADANSONIA DIGITATA SEED OIL; PURSLANE; GLYCYRRHIZINATE DIPOTASSIUM; HAMAMELIS VIRGINIANA WHOLE; BERGAMOT OIL; ORANGE OIL; GRAPEFRUIT OIL; OAT; ROSEMARY OIL; LEMON OIL; WHEAT SPROUT; BROCCOLI SPROUT; BEAN SPROUT; LAVENDER OIL; CERAMIDE 3; MADECASSOSIDE; ALFALFA TOP; EUCALYPTUS OIL; GARDEN CRESS SPROUT; SOYBEAN; SAFFLOWER; CEDRUS ATLANTICA BARK OIL; PELARGONIUM GRAVEOLENS FLOWER OIL; CLOVE; ANGELICA GIGAS ROOT; BUCKWHEAT; THYME; 1,2-HEXANEDIOL; MAGNOLIA X ALBA FLOWER OIL; STYRAX BENZOIN RESIN; CHAMOMILE FLOWER OIL; ROSA RUGOSA FLOWER BUD; CITRUS SINENSIS FLOWER OIL

Drug Facts

ACTIVE INGREDIENT

DIMETHICONE 1.00%

PURPOSE

Skin Protectant

INDICATIONS AND USAGE

Helps to prevent dehydration of skin

DOSAGE AND ADMINISTRATION

Apply liberally as needed onto skin

WARNINGS

For external use only.
Do not use on damaged or broken skin.
When using this product, keep out of eyes. Rinse with water to remove.
Stop using and ask a doctor if rash occurs.

KEEP OUT OF REACH OF CHILDREN

Keep out of reach of the children. If product is swallowed, get medical help or contact a poison control center right away.

INACTIVE INGREDIENT

Centella Asiatica Leaf Water, Purified Water, Water, Glycerin, Centella Asiatica Extract, Butylene Glycol , Butylene Glycol Dicaprylate/Dicaprate, Sunflower Seed Oil, Caprylic/Capric Triglyceride, Dipropylene Glycol, Squalane, Sorbitan Stearate, Beeswax, Cetyl Alcohol, Stearyl Alcohol, Cyclopentasiloxane, Betaine, Macadamia Seed Oil, Cyclohexasiloxane, Shea Butter, Cetearyl Olivate, Polysorbate 60, Caprylyl Glycol, Sorbitan Olivate, Polysorbate 80, Isohexadecane, Sodium Acrylate/Sodium Acryloyldimethyl Taurate Copolymer, Carbomer, Arginine, Allantoin, Caprylhydroxamic Acid, Tocopheryl Acetate, Tremella Fuciformis (Mushroom) Extract, Olive Oil, Asiaticoside, Avocado Oil, Punica Granatum Seed Oil, Hippophae Rhamnoides Fruit Extract, Β-Glucan, Adansonia Digitata Seed Oil, Portulaca Oleracea Extract, Dipotassium Glycyrrhizate, Witch Hazel Water, Citrus Aurantium Bergamia (Bergamot) Fruit Oil, Citrus Aurantium Dulcis (Orange) Peel Oil, Orange Oil, Citrus Paradisi (Grapefruit) Peel Oil, Avena Sativa (Oat) Kernel Extract, Rosemary Leaf Oil, Citrus Lemon Peel Oil, Triticum Vulgare (Wheat) Sprout Extract, Brassica Napus Sprout Extract, Brassica Oleracea Italica (Broccoli) Sprout Extract, Phaseolus Radiatus Sprout Extract, Lavender Oil, Ceramide 3, Madecassoside, Medicago Sativa (Alfalfa) Sprout Extract, Eucalyptus Globulus Leaf Oil, Lepidium Sativum Sprout Extract, Glycine Soja (Soybean) Sprout Extract, Carthamus Tinctorius (Safflower) Sprout Extract, Cedrus Atlantica Bark Oil, Pelargonium Graveolens Flower Oil, Trifolium Repens Sprout Extract, Eugenia Caryophylus (Clove) Bud Extract, Angelica Gigas Sprout Extract, Poltgonum Fagopyrum (Buckwheat) Sporout Extract, Thymus Vulgaris (Thyme) Extract, Buddleja Davidii Extract, 1,2-Hexanediol, Michelia Alba Flower Oil, Styrax Benzoin Resin Extract, Chamomilla Recutita (Matricaria) Flower Oil, Rose Flower Oil, Orange Flower Oil